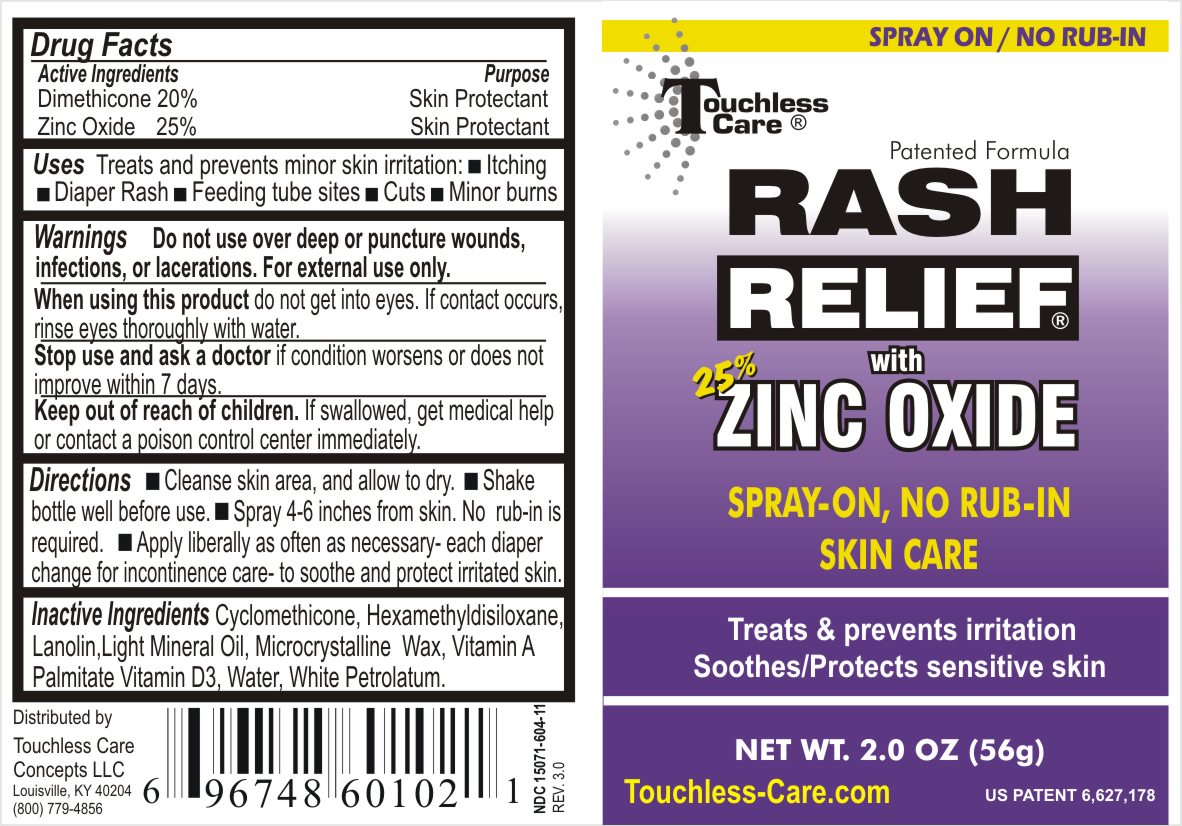 DRUG LABEL: Rash Relief
NDC: 15071-604 | Form: SPRAY
Manufacturer: Touchless Care Concepts LLC
Category: otc | Type: HUMAN OTC DRUG LABEL
Date: 20111018

ACTIVE INGREDIENTS: Zinc Oxide 25 g/100 g; Dimethicone 20 g/100 g
INACTIVE INGREDIENTS: Mineral Oil; Cyclomethicone; Lanolin; Microcrystalline Wax; Hexamethyldisiloxane; Water; Cholecalciferol; Vitamin A Palmitate; Petrolatum 

RASH RELIEF

Active Ingredients

Dimethicone 20%

Zinc Oxide 25%

Purpose

Skin Protectant

Uses: Treats and prevents minor skin irritation - itching - diaper rash - feeding tubes sites, or lacerations.

Warnings

- Do not use over deep or puncture wounds, infections, or lacerations. For external use only.

- When using this product do not get into eyes. If contact occurs, rinse eyes throughout with water.

- Stop use and ask a doctor if condition worsens or does not improve with 7 days.

Directions

- Cleanse skin area, and allow to dry.

- Shake bottle well before use.

- Spray 4-6 inches from skin. No rub-in is required.

- Apply liberally as often as necessary- each diaper change with incontinence care- to soothe and protect irritated skin.

Inactive Ingredients

Cyclomethicone, Hexamethyldisiloxane, Lanolin, Light Mineral Oil, Microcrystalline Wax, Vitamin A Palmitate, Vitamin D3, Water, White Petrolatum

INDICATIONS AND USAGE

Uses: Treats and prevents minor skin irritation - itching - diaper rash - feeding tubes sites, or lacerations.

- Keep out of reach of children. If swallowed, get medical help or contact a local poison control center immediately.